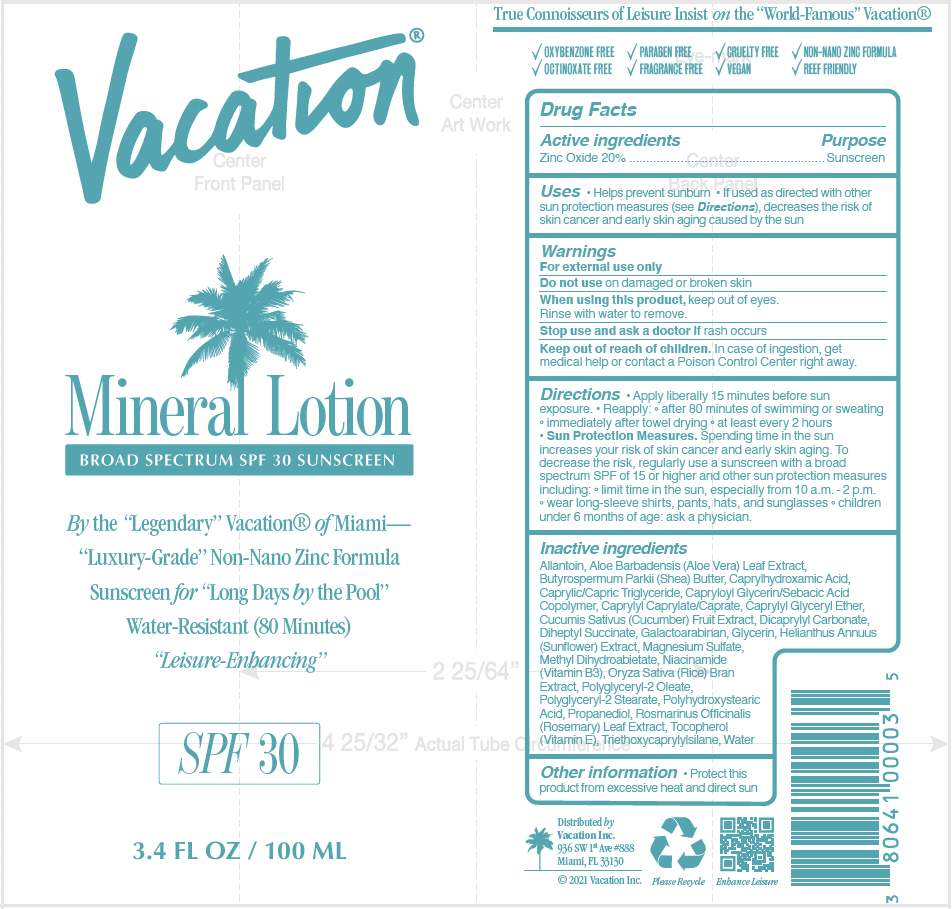 DRUG LABEL: VACATION MINERAL BROAD SPECTRUM SPF 30 SUNSCREEN
NDC: 80641-002 | Form: LOTION
Manufacturer: Vacation Inc.
Category: otc | Type: HUMAN OTC DRUG LABEL
Date: 20210505

ACTIVE INGREDIENTS: Zinc Oxide 20 g/100 mL
INACTIVE INGREDIENTS: Allantoin; Aloe Vera Leaf; Shea Butter; Caprylhydroxamic Acid; Medium-Chain Triglycerides; CAPRYLOYL GLYCERIN/SEBACIC ACID COPOLYMER (2000 MPA.S); Caprylyl Caprylate/Caprate; Caprylyl Glyceryl Ether; Cucumber; Dicaprylyl Carbonate; Diheptyl Succinate; Galactoarabinan; Glycerin; Helianthus Annuus Flowering Top; Magnesium Sulfate, Unspecified Form; Methyl Dihydroabietate; NIACIN; Rice Bran; Polyglyceryl-2 Oleate; Polyglyceryl-2 Stearate; Propanediol; Rosemary; .Alpha.-Tocopherol; Triethoxycaprylylsilane; Water

VACATION® MINERAL BROAD SPECTRUM SPF 30 SUNSCREEN

Drug Facts

Active ingredients

Zinc Oxide 20%

Purpose

Sunscreen

Uses

- Helps prevent sunburn
- If used as directed with other sun protection measures (see Directions), decreases the risk of skin cancer and early skin aging caused by the sun

Warnings

For external use only

Do not use on damaged or broken skin

When using this product, keep out of eyes. Rinse with water to remove.

Stop use and ask a doctor if rash occurs

Keep out of reach of children. In case of ingestion, get medical help or contact a Poison Control Center right away.

Directions

- Apply liberally 15 minutes before sun exposure.
- Reapply:
  - after 80 minutes of swimming or sweating
  - immediately after towel drying
  - at least every 2 hours
- Sun Protection Measures. Spending time in the sun increases your risk of skin cancer and early skin aging. To decrease the risk, regularly use a sunscreen with a broad spectrum SPF of 15 or higher and other sun protection measures including:
  - limit time in the sun, especially from 10 a.m. - 2 p.m.
  - wear long-sleeve shirts, pants, hats, and sunglasses
  - children under 6 months of age: ask a physician.

Inactive ingredients

Allantoin, Aloe Barbadensis (Aloe Vera) Leaf Extract, Butyrospermum Parkii (Shea) Butter, Caprylhydroxamic Acid, Caprylic/Capric Triglyceride, Capryloyl Glycerin/Sebacic Acid Copolymer, Caprylyl Caprylate/Caprate, Caprylyl Glyceryl Ether, Cucumis Sativus (Cucumber) Fruit Extract, Dicaprylyl Carbonate, Diheptyl Succinate, Galactoarabinan, Glycerin, Helianthus Annuus (Sunflower) Extract, Magnesium Sulfate, Methyl Dihydroabietate, Niacinamide (Vitamin B3), Oryza Sativa (Rice) Bran Extract, Polyglyceryl-2 Oleate, Polyglyceryl-2 Stearate, Polyhydroxystearic Acid, Propanediol, Rosmarinus Officinalis (Rosemary) Leaf Extract, Tocopherol (Vitamin E), Triethoxycaprylylsilane, Water

Other information

- Protect this product from excessive heat and direct sun

Distributed by
Vacation Inc.
936 SW 1st Ave #888
Miami, FL 33130

PRINCIPAL DISPLAY PANEL - 100 ML Tube Label

Vacation®

Mineral Lotion
BROAD SPECTRUM SPF 30 SUNSCREEN

By the "Legendary" Vacation® of Miami—
"Luxury-Grade" Non-Nano Zinc Formula
Sunscreen for "Long Days by the Pool"
Water-Resistant (80 Minutes)
"Leisure-Enhancing"

SPF 30

3.4 FL OZ / 100 ML